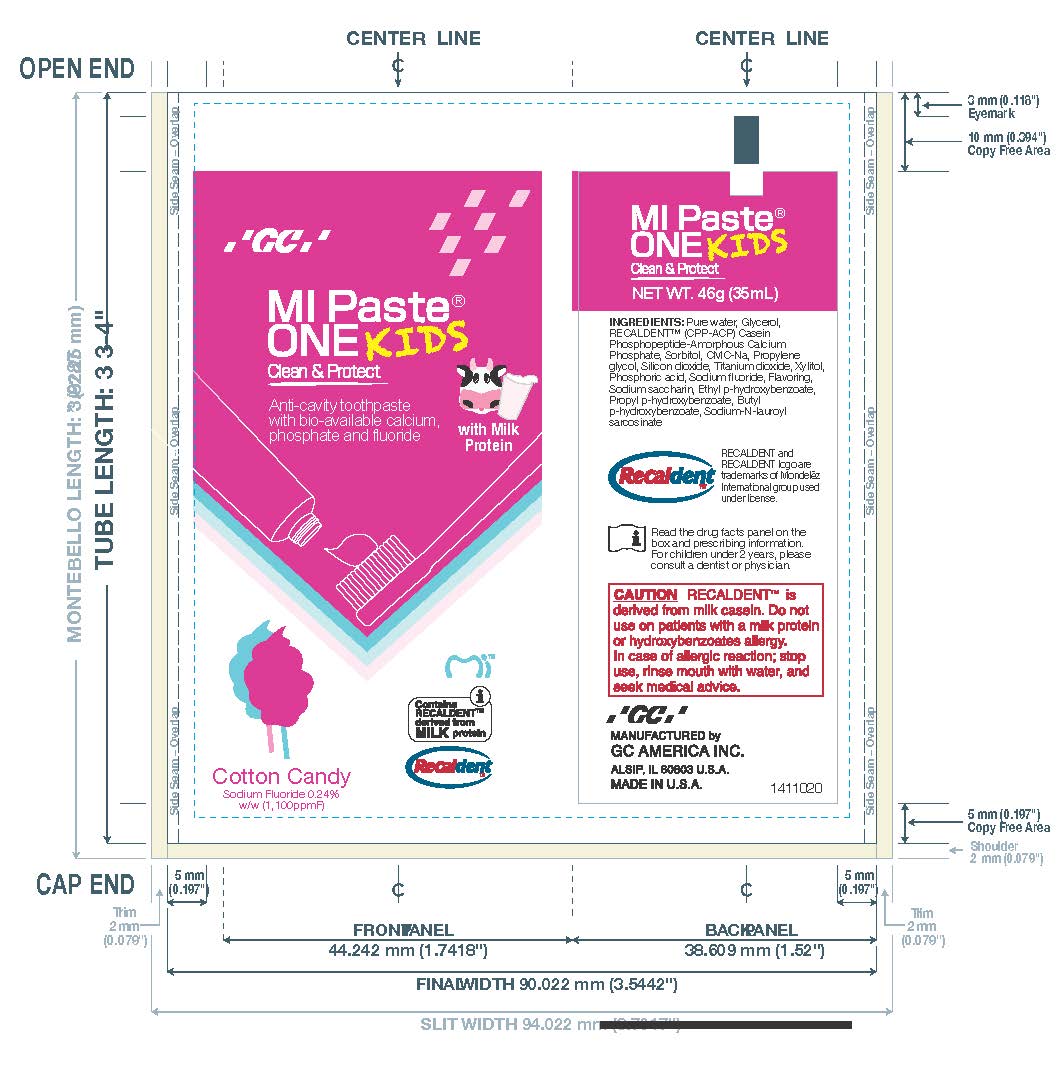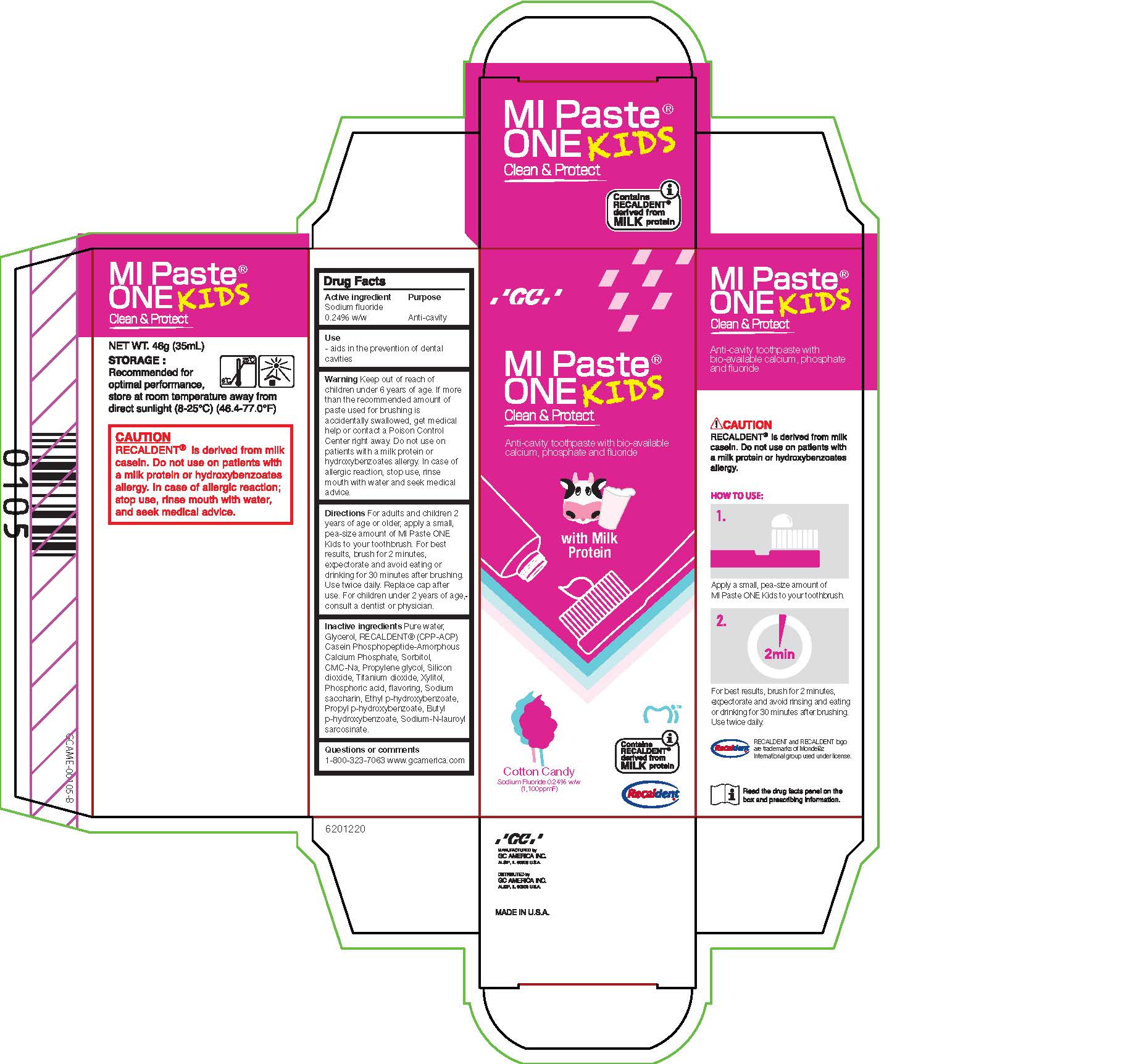 DRUG LABEL: MIPaste One Kids Cotton Candy
NDC: 61596-102 | Form: PASTE, DENTIFRICE
Manufacturer: GC America Inc.	
Category: otc | Type: HUMAN OTC DRUG LABEL
Date: 20251219

ACTIVE INGREDIENTS: SODIUM FLUORIDE 0.24 g/100 g
INACTIVE INGREDIENTS: BUTYLPARABEN; GLYCERIN; XYLITOL; SODIUM LAUROYL SARCOSINATE; PHOSPHORIC ACID; SACCHARIN SODIUM; WATER; PROPYLPARABEN; PROPYLENE GLYCOL; CARBOXYMETHYLCELLULOSE SODIUM, UNSPECIFIED; TITANIUM DIOXIDE; ETHYLPARABEN; CALCIUM PHOSPHATE, UNSPECIFIED FORM; SILICON DIOXIDE; SORBITOL

MIPaste One Kids Cotton Candy

DOSAGE AND ADMINISTRATION

Directions For adults and children 2
years of age or older, apply a small,
pea-size amount of MI Paste ONE
Kids to your toothbrush. For best
results, brush for 2 minutes,
expectorate and avoid eating or
drinking for 30 minutes after brushing.
Use twice daily. Replace cap after
use. For children under 2 years of age,
consult a dentist or physician.

WARNINGS

Warning Keep out of reach of
children under 6 years of age. If more
than the recommended amount of
paste used for brushing is
accidentally swallowed, get medical
help or contact a Poison Control
Center right away. Do not use on
patients with a milk protein or
hydroxybenzoates allergy. In case of
allergic reaction, stop use, rinse
mouth with water and seek medical
advice.

Inactive ingredients Pure water,
Glycerol, RECALDENT CPP-ACP
Casein Phosphopeptide-Amorphous
Calcium Phosphate, Sorbitol,
CMC-Na, Propylene glycol, Silicon
dioxide, Titanium dioxide, Xylitol,
Phosphoric acid, Flavoring, Sodium
saccharin, Ethyl p-hydroxybenzoate,
Propyl p-hydroxybenzoate, Butyl
p-hydroxybenzoate, Sodium-N-lauroyl
sarcosinate.

Use
- aids in the prevention of dental
cavities

Warning Keep out of reach of
children under 6 years of age. If more
than the recommended amount of
paste used for brushing is
accidentally swallowed, get medical
help or contact a Poison Control
Center right away. Do not use on
patients with a milk protein or
hydroxybenzoates allergy. In case of
allergic reaction, stop use, rinse
mouth with water and seek medical
advice.

Purpose: Anticavity

Active ingredient
Sodium Fluoride
0.24% w/w